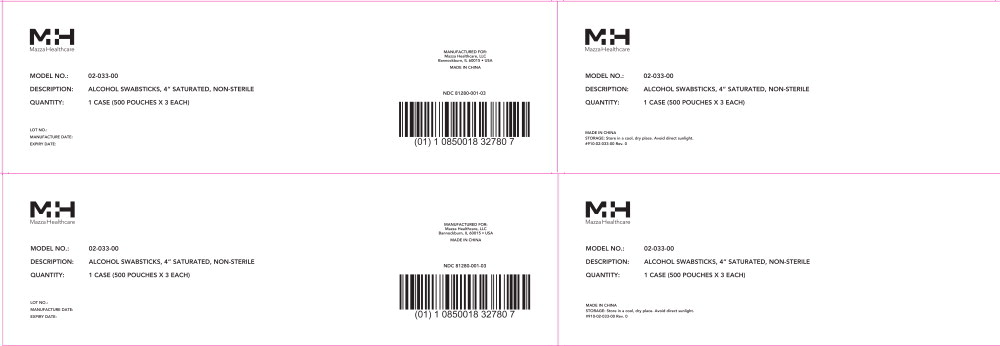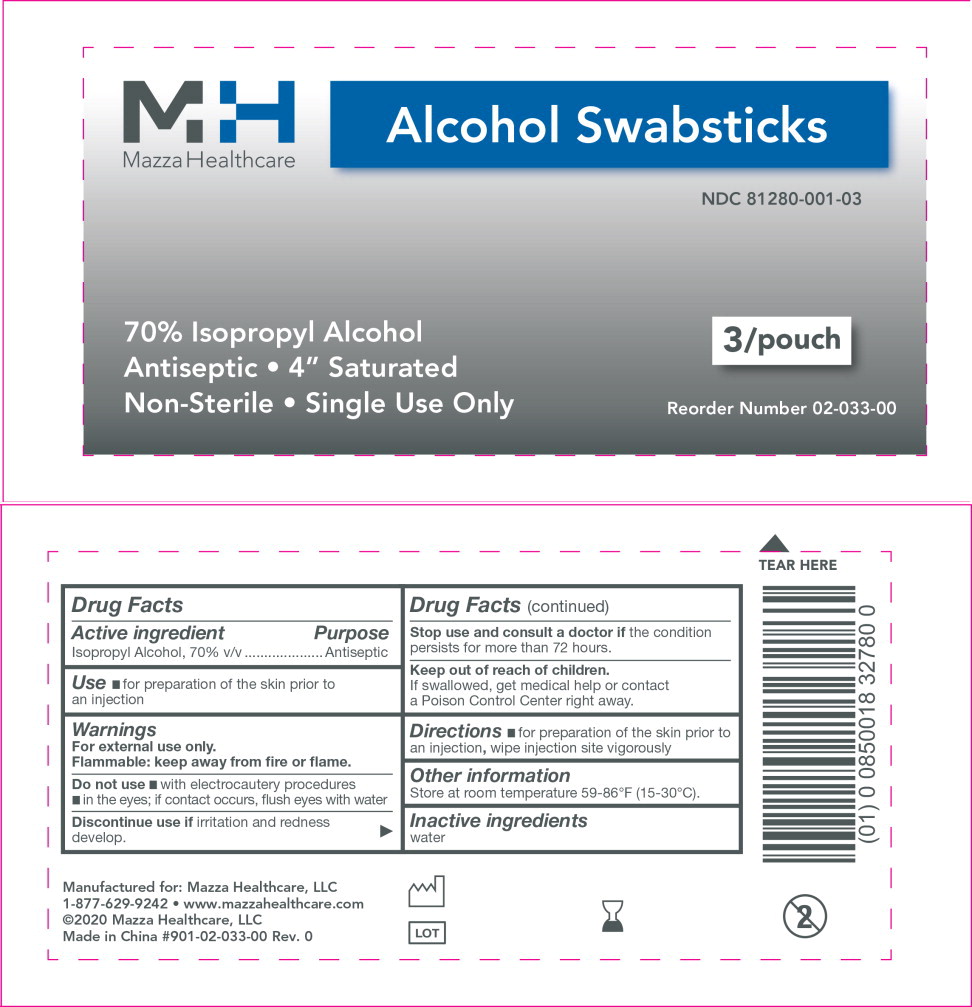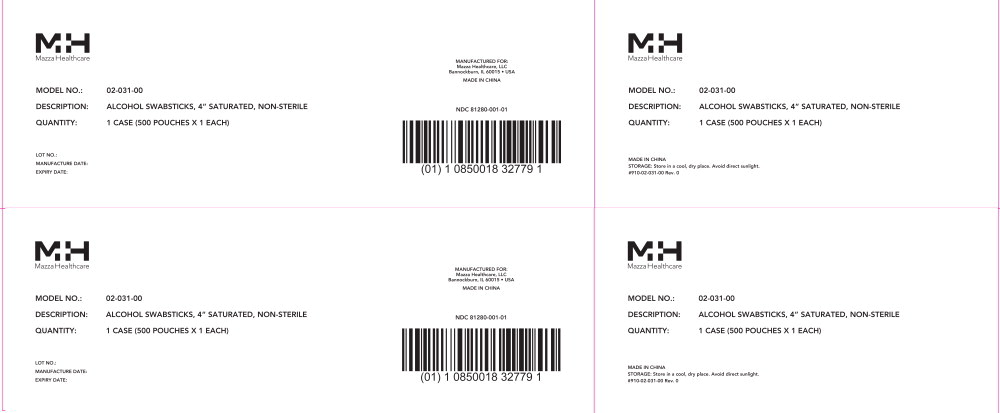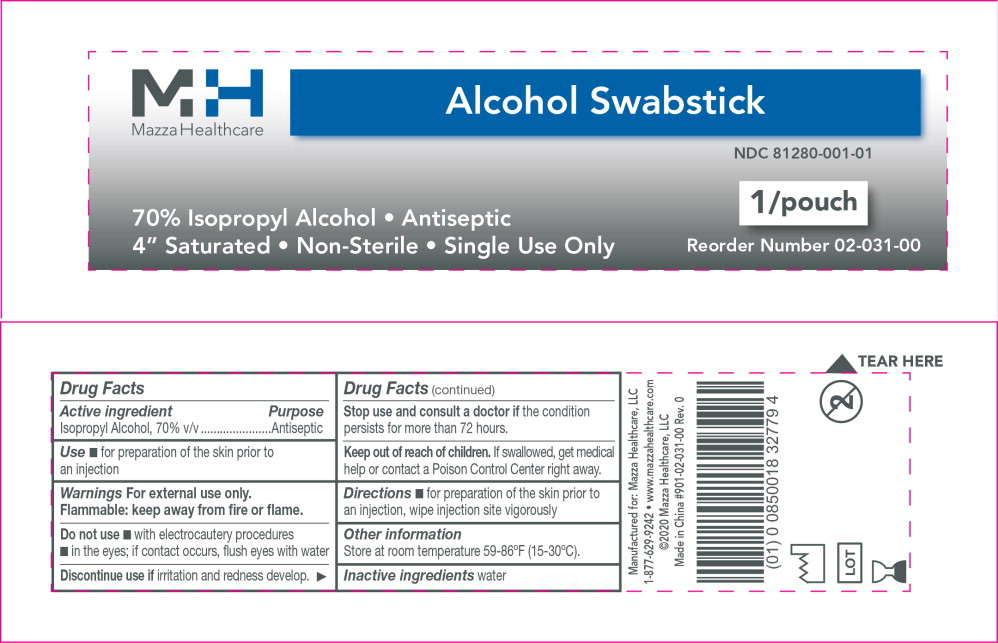 DRUG LABEL: Isopropyl Alcohol
NDC: 81280-001 | Form: SWAB
Manufacturer: Mazza Healthcare, LLC
Category: otc | Type: HUMAN OTC DRUG LABEL
Date: 20241121

ACTIVE INGREDIENTS: Isopropyl Alcohol 70 mL/100 mL
INACTIVE INGREDIENTS: Water

Drug Facts

Active ingredient

Isopropyl Alcohol, 70% v/v

Purpose

Antiseptic

Use

- for preparation of the skin prior to an injection

Warnings

For external use only.

Flammable: keep away from fire or flame.

Do not use

- with electrocautery procedures
- in the eyes; if contact occurs, flush eyes with water

Discontinue use if irritation and redness develop.

Stop use and consult a doctor if the condition persists for more than 72 hours.

Keep out of reach of children. If swallowed, get medical help or contact a Poison Control Center right away.

Directions

- for preparation of the skin prior to an injection, wipe injection site vigorously

Other information

Store at room temperature 59-86ºF (15-30ºC).

Inactive ingredients

water

Mazza Healthcare, LLC
1-877-629-9242

Principal Display Panel - 500 Pouch Carton Label

MH

Mazza Healthcare

MODEL NO.: 02-033-00

DESCRIPTION: ALCOHOL SWABSTICKS, 4” SATURATED, NON-STERILE

QUANTITY: 1 CASE (500 POUCHES X 3 EACH)

LOT NO.:

MANUFACTURE DATE:

EXPIRY DATE:

MANUFACTURED FOR:

Mazza Healthcare, LLC

Bannockburn, IL 60015 • USA

MADE IN CHINA

NDC 81280-001-03

Principal Display Panel - 3 Applicators Pouch Label

MH

Mazza Healthcare

Alcohol Swabsticks

NDC 81280-001-03

70% Isopropyl Alcohol • Antiseptic

4” Saturated • Non-Sterile • Single Use Only

3/pouch

Reorder Number 02-033-00

Principal Display Panel - 500 Pouch Carton Label

MH

Mazza Healthcare

MODEL NO.: 02-031-00

DESCRIPTION: ALCOHOL SWABSTICKS, 4” SATURATED, NON-STERILE

QUANTITY: 1 CASE (500 POUCHES X 1 EACH)

LOT NO.:

MANUFACTURE DATE:

EXPIRY DATE:

MANUFACTURED FOR:

Mazza Healthcare, LLC

Bannockburn, IL 60015 • USA

MADE IN CHINA

NDC 81280-001-01

Principal Display Panel - 1 Applicator Pouch Label

MH

Mazza Healthcare

Alcohol Swabstick

NDC 81280-001-01

70% Isopropyl Alcohol • Antiseptic

4” Saturated • Non-Sterile • Single Use Only

1/pouch

Reorder Number 02-031-00